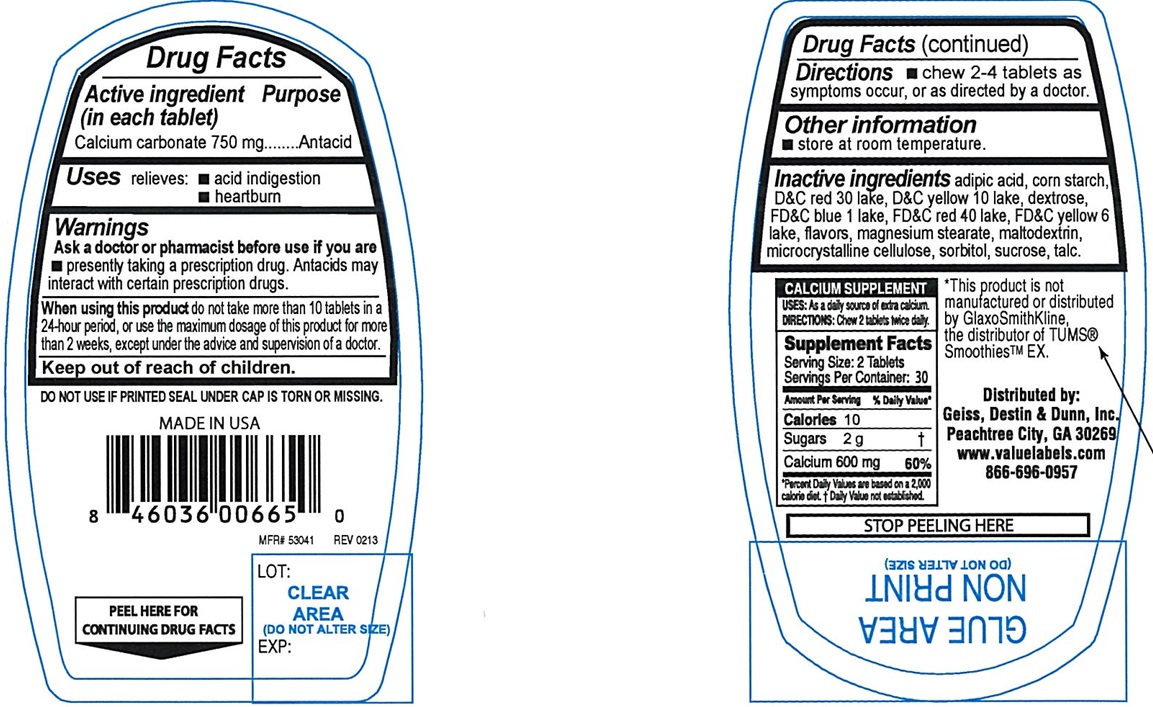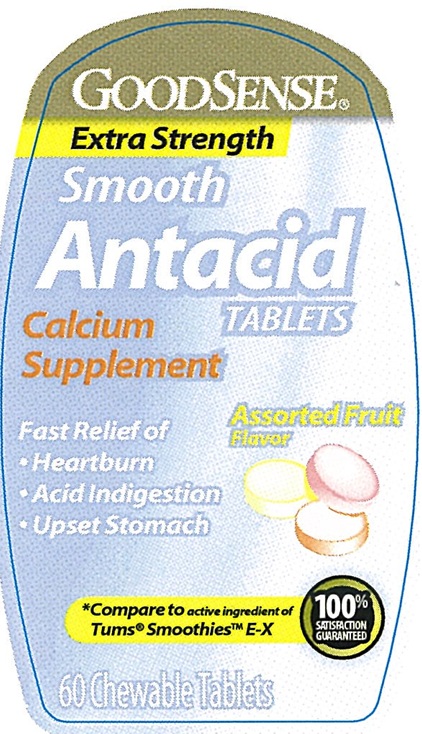 DRUG LABEL: Extra Strength Smooth Antacid Assorted Fruits
NDC: 50804-179 | Form: TABLET, CHEWABLE
Manufacturer: Good Sense (Geiss, Destin & Dunn, Inc.)
Category: otc | Type: Human OTC Drug Label
Date: 20250228

ACTIVE INGREDIENTS: CALCIUM CARBONATE 750 mg/1 1
INACTIVE INGREDIENTS: ADIPIC ACID; STARCH, CORN; DEXTROSE, UNSPECIFIED FORM; FD&C BLUE NO. 1 ALUMINUM LAKE; FD&C RED NO. 40 ALUMINUM LAKE; MAGNESIUM STEARATE; MALTODEXTRIN; SUCROSE; TALC; SORBITOL; MICROCRYSTALLINE CELLULOSE; D&C RED NO. 30 ALUMINUM LAKE; D&C YELLOW NO. 10 ALUMINUM LAKE; FD&C YELLOW NO. 6 ALUMINUM LAKE

Extra Strength Smooth Antacid Assorted Fruit Chewable Tablets

ACTIVE INGREDIENT (in each tablet)

Calcium carbonate 750 mg

PURPOSE

Antacid

USE(S)

relieves:

- acid indigestion
- heartburn

WARNINGS

.

ASK A DOCTOR OR PHARMACIST BEFORE USE IF YOU ARE

- presently taking a prescription drug. Antacids may interact with certain prescription drugs.

WHEN USING THIS PRODUCT

do not take more than 10 tablets in a 24-hour period, or use the maximum dosage of this product for more than 2 weeks, except under the advice and supervision of a doctor.

IF PREGNANT OR BREAST FEEDING,

ask a health professional before use.

KEEP OUT OF REACH OF CHILDREN

.

DIRECTIONS

- adults and children 12 years of age and over: chew 2-4 tablets as symptoms occur, or as directed by a doctor.

OTHER INFORMATION

- store at room temperature.

INACTIVE INGREDIENTS

adipic acid, corn starch, D&C red 30 lake, D&C yellow 10 lake, dextrose, FD&C blue 1 lake, FD&C red 40 lake, FD&C yellow 6 lake, flavors, magnesium stearate, maltodextrin, microcrystalline cellulose, sorbitol, sucrose, talc.

PRINCIPAL DISPLAY PANEL

GOODSENSE®
Extra Strength
Smooth
Antacid

Tablets
Calcium Supplement
Fast Relief of

- Heartburn
- Acid Indigestion
- Upset Stomach

Assorted Fruit Flavors

*Compare to active ingredient of Tums® Smoothies™ E-X

60 CHEWABLE TABLETS